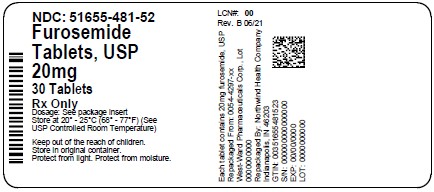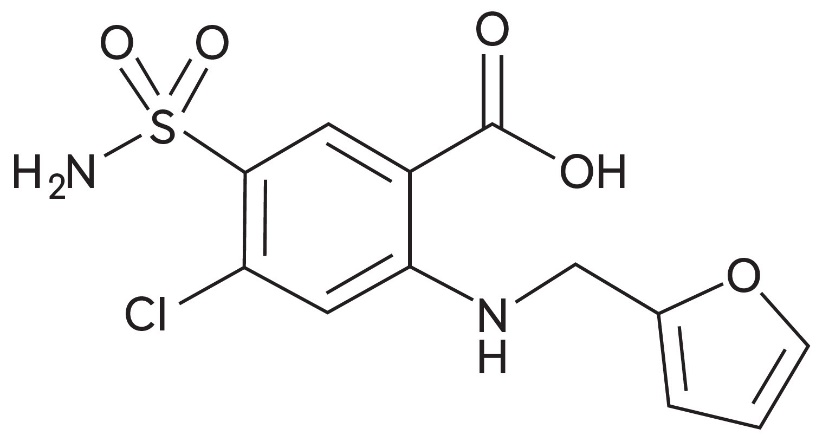 DRUG LABEL: Furosemide
NDC: 51655-481 | Form: TABLET
Manufacturer: Northwind Health Company, LLC
Category: prescription | Type: HUMAN PRESCRIPTION DRUG LABEL
Date: 20260101

ACTIVE INGREDIENTS: FUROSEMIDE 20 mg/1 1
INACTIVE INGREDIENTS: SILICON DIOXIDE; LACTOSE MONOHYDRATE; MICROCRYSTALLINE CELLULOSE; STARCH, CORN; SODIUM LAURYL SULFATE; SODIUM STARCH GLYCOLATE TYPE A POTATO; STEARIC ACID

Furosemide Tablets, USP and Furosemide Oral Solution, USP
Rx only

WARNING

Furosemide is a potent diuretic which, if given in excessive amounts, can lead to a profound diuresis with water and electrolyte depletion. Therefore, careful medical supervision is required and dose and dose schedule must be adjusted to the individual patient’s needs (See DOSAGE AND ADMINISTRATION).

DESCRIPTION

Each tablet for oral administration contains:

- Furosemide, USP . . . . . . . . . . . . . . . . 20 mg, 40 mg and 80 mg

Each mL of Oral Solution for oral administration contains:

- Furosemide, USP . . . . . . . . . . . . . . . . 10 mg per mL or 8 mg (40 mg per 5 mL)

Furosemide is a diuretic which is an anthranilic acid derivative. Chemically, it is 4-chloro- N-furfuryl-5-sulfamoylanthranilic acid. Furosemide is a white to slightly yellow, crystalline powder. It is practically insoluble in water; freely soluble in acetone, dimethylformamide and in solutions of alkali hydroxides; soluble in methanol; sparingly soluble in alcohol; slightly soluble in ether; very slightly soluble in chloroform. The CAS Registry Number is 54-31-9.

The structural formula is as follows:

C12H11ClN2O5S M.W. 330.74

Furosemide Tablets, USP are available for oral administration containing 20 mg, 40 mg or 80 mg of Furosemide, USP. The tablets meet Dissolution Test 1. Each tablet contains the following inactive ingredients: colloidal silicon dioxide, corn starch, lactose monohydrate, microcrystalline cellulose, pregelatinized starch, purified water, sodium lauryl sulfate, sodium starch glycolate and stearic acid.

Furosemide Oral Solution, USP is also available for oral administration containing either 10 mg per mL or 40 mg per 5 mL. The oral solution contains the following inactive ingredients: D and C Yellow No. 10, FD and C Yellow No. 6, flavors, potassium carbonate 1½ hydrate, propylene glycol, purified water and sorbitol solution. The 10 mg/mL solution is orange flavored and contains prosweet liquid and saccharin sodium. The 40 mg/5 mL solution is pineapple-peach flavored and contains sweet tone.

CLINICAL PHARMACOLOGY

Investigations into the mode of action of furosemide have utilized micropuncture studies in rats, stop flow experiments in dogs and various clearance studies in both humans and experimental animals. It has been demonstrated that furosemide inhibits primarily the absorption of sodium and chloride not only in the proximal and distal tubules but also in the loop of Henle. The high degree of efficacy is largely due to the unique site of action. The action on the distal tubule is independent of any inhibitory effect on carbonic anhydrase and aldosterone.

Recent evidence suggests that furosemide glucuronide is the only or at least the major biotransformation product of furosemide in man. Furosemide is extensively bound to plasma proteins, mainly to albumin. Plasma concentrations ranging from 1 mcg/mL to 400 mcg/mL are 91% to 99% bound in healthy individuals. The unbound fraction averages 2.3% to 4.1% at therapeutic concentrations.

The onset of diuresis following oral administration is within 1 hour. The peak effect occurs within the first or second hour. The duration of diuretic effect is 6 to 8 hours.

In fasted normal men, the mean bioavailability of furosemide from Furosemide Tablets and Furosemide Oral Solution is 64% and 60%, respectively, of that from an intravenous injection of the drug. Although furosemide is more rapidly absorbed from the oral solution (50 minutes) than from the tablet (87 minutes), peak plasma levels and area under the plasma concentration-time curves do not differ significantly. Peak plasma concentrations increase with increasing dose but times-to-peak do not differ among doses. The terminal half-life of furosemide is approximately 2 hours.

Significantly more furosemide is excreted in urine following the IV injection than after the tablet or oral solution. There are no significant differences between the two oral formulations in the amount of unchanged drug excreted in urine.

Geriatric Population

Furosemide binding to albumin may be reduced in elderly patients. Furosemide is predominantly excreted unchanged in the urine. The renal clearance of furosemide after intravenous administration in older healthy male subjects (60 to 70 years of age) is statistically significantly smaller than in younger healthy male subjects (20 to 35 years of age). The initial diuretic effect of furosemide in older subjects is decreased relative to younger subjects (See PRECAUTIONS: Geriatric Use).

INDICATIONS AND USAGE

Edema

Furosemide is indicated in adults and pediatric patients for the treatment of edema associated with congestive heart failure, cirrhosis of the liver and renal disease, including the nephrotic syndrome. Furosemide is particularly useful when an agent with greater diuretic potential is desired.

Hypertension

Oral furosemide may be used in adults for the treatment of hypertension alone or in combination with other antihypertensive agents. Hypertensive patients who cannot be adequately controlled with thiazides will probably also not be adequately controlled with furosemide alone.

CONTRAINDICATIONS

Furosemide is contraindicated in patients with anuria and in patients with a history of hypersensitivity to furosemide.

WARNINGS

In patients with hepatic cirrhosis and ascites, furosemide therapy is best initiated in the hospital. In hepatic coma and in states of electrolyte depletion, therapy should not be instituted until the basic condition is improved. Sudden alterations of fluid and electrolyte balance in patients with cirrhosis may precipitate hepatic coma; therefore, strict observation is necessary during the period of diuresis. Supplemental potassium chloride and, if required, an aldosterone antagonist are helpful in preventing hypokalemia and metabolic alkalosis.

If increasing azotemia and oliguria occur during treatment of severe progressive renal disease, furosemide should be discontinued.

Cases of tinnitus and reversible or irreversible hearing impairment and deafness have been reported. Reports usually indicate that furosemide ototoxicity is associated with rapid injection, severe renal impairment, the use of higher than recommended doses, hypoproteinemia or concomitant therapy with aminoglycoside antibiotics, ethacrynic acid, or other ototoxic drugs. If the physician elects to use high dose parenteral therapy, controlled intravenous infusion is advisable (for adults, an infusion rate not exceeding 4 mg furosemide per minute has been used) (See PRECAUTIONS: Drug Interactions).

PRECAUTIONS

General

Excessive diuresis may cause dehydration and blood volume reduction with circulatory collapse and possibly vascular thrombosis and embolism, particularly in elderly patients. As with any effective diuretic, electrolyte depletion may occur during furosemide therapy, especially in patients receiving higher doses and a restricted salt intake. Hypokalemia may develop with furosemide, especially with brisk diuresis, inadequate oral electrolyte intake, when cirrhosis is present, or during concomitant use of corticosteroids, ACTH, licorice in large amounts, or prolonged use of laxatives. Digitalis therapy may exaggerate metabolic effects of hypokalemia, especially myocardial effects.

All patients receiving furosemide therapy should be observed for these signs or symptoms of fluid or electrolyte imbalance (hyponatremia, hypochloremic alkalosis, hypokalemia, hypomagnesemia or hypocalcemia): dryness of mouth, thirst, weakness, lethargy, drowsiness, restlessness, muscle pains or cramps, muscular fatigue, hypotension, oliguria, tachycardia, arrhythmia, or gastrointestinal disturbances such as nausea and vomiting. Increases in blood glucose and alterations in glucose tolerance tests (with abnormalities of the fasting and 2-hour postprandial sugar) have been observed, and rarely, precipitation of diabetes mellitus has been reported.

In patients with severe symptoms of urinary retention (because of bladder emptying disorders, prostatic hyperplasia, urethral narrowing), the administration of furosemide can cause acute urinary retention related to increased production and retention of urine. Thus, these patients require careful monitoring, especially during the initial stages of treatment.

In patients at high risk for radiocontrast nephropathy, furosemide can lead to a higher incidence of deterioration in renal function after receiving radiocontrast compared to high-risk patients who received only intravenous hydration prior to receiving radiocontrast.

In patients with hypoproteinemia (e.g., associated with nephrotic syndrome), the effect of furosemide may be weakened and its ototoxicity potentiated.

Asymptomatic hyperuricemia can occur and gout may rarely be precipitated.

Patients allergic to sulfonamides may also be allergic to furosemide. The possibility exists of exacerbation or activation of systemic lupus erythematosus.

As with many other drugs, patients should be observed regularly for the possible occurrence of blood dyscrasias, liver or kidney damage, or other idiosyncratic reactions.

Information for Patients

Patients receiving furosemide should be advised that they may experience symptoms from excessive fluid and/or electrolyte losses. The postural hypotension that sometimes occurs can usually be managed by getting up slowly. Potassium supplements and/or dietary measures may be needed to control or avoid hypokalemia.

Patients with diabetes mellitus should be told that furosemide may increase blood glucose levels and thereby affect urine glucose tests. The skin of some patients may be more sensitive to the effects of sunlight while taking furosemide.

Hypertensive patients should avoid medications that may increase blood pressure, including over-the-counter products for appetite suppression and cold symptoms.

Laboratory Tests

Serum electrolytes (particularly potassium), CO2, creatinine and BUN should be determined frequently during the first few months of furosemide therapy and periodically thereafter. Serum and urine electrolyte determinations are particularly important when the patient is vomiting profusely or receiving parenteral fluids. Abnormalities should be corrected or the drug temporarily withdrawn. Other medications may also influence serum electrolytes.

Reversible elevations of BUN may occur and are associated with dehydration, which should be avoided, particularly in patients with renal insufficiency.

Urine and blood glucose should be checked periodically in diabetics receiving furosemide, even in those suspected of latent diabetes.

Furosemide may lower serum levels of calcium (rarely cases of tetany have been reported) and magnesium. Accordingly, serum levels of these electrolytes should be determined periodically.

In premature infants furosemide may precipitate nephrocalcinosis/nephrolithiasis, therefore renal function must be monitored and renal ultrasonography performed (See PRECAUTIONS: Pediatric Use).

Drug Interactions

Furosemide may increase the ototoxic potential of aminoglycoside antibiotics, especially in the presence of impaired renal function. Except in life-threatening situations, avoid this combination.

Furosemide should not be used concomitantly with ethacrynic acid because of the possibility of ototoxicity. Patients receiving high doses of salicylates concomitantly with furosemide, as in rheumatic disease, may experience salicylate toxicity at lower doses because of competitive renal excretory sites.

There is a risk of ototoxic effects if cisplatin and furosemide are given concomitantly. In addition, nephrotoxicity of nephrotoxic drugs such as cisplatin may be enhanced if furosemide is not given in lower doses and with positive fluid balance when used to achieve forced diuresis during cisplatin treatment.

Furosemide has a tendency to antagonize the skeletal muscle-relaxing effect of tubocurarine and may potentiate the action of succinylcholine.

Lithium generally should not be given with diuretics because they reduce lithium’s renal clearance and add a high risk of lithium toxicity.

Furosemide combined with angiotensin-converting enzyme inhibitors or angiotensin II receptor blockers may lead to severe hypotension and deterioration in renal function, including renal failure. An interruption or reduction in the dosage of furosemide, angiotensin-converting enzyme inhibitors, or angiotensin receptor blockers may be necessary.

Potentiation occurs with ganglionic or peripheral adrenergic blocking drugs.

Furosemide may decrease arterial responsiveness to norepinephrine. However, norepinephrine may still be used effectively.

Simultaneous administration of sucralfate and furosemide tablets may reduce the natriuretic and antihypertensive effects of furosemide. Patients receiving both drugs should be observed closely to determine if the desired diuretic and/or antihypertensive effect of furosemide is achieved. The intake of furosemide and sucralfate should be separated by at least two hours.

In isolated cases, intravenous administration of furosemide within 24 hours of taking chloral hydrate may lead to flushing, sweating attacks, restlessness, nausea, increase in blood pressure, and tachycardia. Use of furosemide concomitantly with chloral hydrate is therefore not recommended.

Phenytoin interferes directly with renal action of furosemide. There is evidence that treatment with phenytoin leads to decreased intestinal absorption of furosemide, and consequently to lower peak serum furosemide concentrations.

Methotrexate and other drugs that, like furosemide, undergo significant renal tubular secretion may reduce the effect of furosemide. Conversely, furosemide may decrease renal elimination of other drugs that undergo tubular secretion. High-dose treatment of both furosemide and these other drugs may result in elevated serum levels of these drugs and may potentiate their toxicity as well as the toxicity of furosemide.

Furosemide can increase the risk of cephalosporin-induced nephrotoxicity even in the setting of minor or transient renal impairment.

Concomitant use of cyclosporine and furosemide is associated with increased risk of gouty arthritis secondary to furosemide-induced hyperurecemia and cyclosporine impairment of renal urate excretion.

High doses (>80 mg) of furosemide may inhibit the binding of thyroid hormones to carrier proteins and result in transient increase in free thyroid hormones, followed by an overall decrease in total thyroid hormone levels.

One study in six subjects demonstrated that the combination of furosemide and acetylsalicylic acid temporarily reduced creatinine clearance in patients with chronic renal insufficiency. There are case reports of patients who developed increased BUN, serum creatinine and serum potassium levels, and weight gain when furosemide was used in conjunction with NSAIDs.

Literature reports indicate that coadministration of indomethacin may reduce the natriuretic and antihypertensive effects of furosemide in some patients by inhibiting prostaglandin synthesis. Indomethacin may also affect plasma renin levels, aldosterone excretion, and renin profile evaluation. Patients receiving both indomethacin and furosemide should be observed closely to determine if the desired diuretic and/or antihypertensive effect of furosemide is achieved.

Carcinogenesis, Mutagenesis, Impairment of Fertility

Furosemide was tested for carcinogenicity by oral administration in one strain of mice and one strain of rats. A small but significantly increased incidence of mammary gland carcinomas occurred in female mice at a dose 17.5 times the maximum human dose of 600 mg. There were marginal increases in uncommon tumors in male rats at a dose of 15 mg/kg (slightly greater than the maximum human dose) but not at 30 mg/kg.

Furosemide was devoid of mutagenic activity in various strains of Salmonella typhimuriumwhen tested in the presence or absence of an in vitrometabolic activation system, and questionably positive for gene mutation in mouse lymphoma cells in the presence of rat liver S9 at the highest dose tested. Furosemide did not induce sister chromatid exchange in human cells in vitro, but other studies on chromosomal aberrations in human cells in vitrogave conflicting results. In Chinese hamster cells it induced chromosomal damage but was questionably positive for sister chromatid exchange. Studies on the induction by furosemide of chromosomal aberrations in mice were inconclusive. The urine of rats treated with this drug did not induce gene conversion in Saccharomyces cerevisiae.

Furosemide produced no impairment of fertility in male or female rats, at 100 mg/kg/day (the maximum effective diuretic dose in the rat and 8 times the maximal human dose of 600 mg/day).

Pregnancy

Furosemide has been shown to cause unexplained maternal deaths and abortions in rabbits at 2, 4, and 8 times the maximal recommended human dose. There are no adequate and well-controlled studies in pregnant women. Furosemide should be used during pregnancy only if the potential benefit justifies the potential risk to the fetus.

Treatment during pregnancy requires monitoring of fetal growth because of the potential for higher birth weights.

The effects of furosemide on embryonic and fetal development and on pregnant dams were studied in mice, rats and rabbits.

Furosemide caused unexplained maternal deaths and abortions in the rabbit at the lowest dose of 25 mg/kg (two times the maximal recommended human dose of 600 mg/day). In another study, a dose of 50 mg/kg (four times the maximal recommended human dose of 600 mg/day) also caused maternal deaths and abortions when administered to rabbits between Days 12 and 17 of gestation. In a third study, none of the pregnant rabbits survived a dose of 100 mg/kg. Data from the above studies indicate fetal lethality that can precede maternal deaths.

The results of the mouse study and one of the three rabbit studies also showed an increased incidence and severity of hydronephrosis (distention of the renal pelvis and in some cases of the ureters) in fetuses derived from the treated dams as compared with the incidence in fetuses from the control group.

Nursing Mothers

Because it appears in breast milk, caution should be exercised when furosemide is administered to a nursing mother.

Furosemide may inhibit lactation.

Pediatric Use

In premature infants furosemide may precipitate nephrocalcinosis/nephrolithiasis. Nephrocalcinosis/nephrolithiasis has also been observed in children under 4 years of age with no history of prematurity who have been treated chronically with furosemide. Monitor renal function, and renal ultrasonography should be considered, in pediatric patients receiving furosemide.

If furosemide is administered to premature infants during the first weeks of life, it may increase the risk of persistence of patent ductus arteriosus.

Geriatric Use

Controlled clinical studies of furosemide did not include sufficient numbers of subjects aged 65 and over to determine whether they respond differently from younger subjects. Other reported clinical experience has not identified differences in responses between the elderly and younger patients. In general, dose selection for the elderly patient should be cautious, usually starting at the low end of the dosing range, reflecting the greater frequency of decreased hepatic, renal, or cardiac function, and of concomitant disease or other drug therapy.

This drug is known to be substantially excreted by the kidney, and the risk of toxic reactions to this drug may be greater in patients with impaired renal function. Because elderly patients are more likely to have decreased renal function, care should be taken in dose selection and it may be useful to monitor renal function (See PRECAUTIONS: Generaland DOSAGE AND ADMINISTRATION).

ADVERSE REACTIONS

Adverse reactions are categorized below by organ system and listed by decreasing severity.

Gastrointestinal System Reactions:

1. hepatic encephalopathy in patients with hepatocellular insufficiency
2. pancreatitis
3. jaundice (intrahepatic cholestatic jaundice)
4. increased liver enzymes
5. anorexia
6. oral and gastric irritation
7. cramping
8. diarrhea
9. constipation
10. nausea
11. vomiting

Systemic Hypersensitivity Reactions:

1. severe anaphylactic or anaphylactoid reactions (e.g. with shock)
2. systemic vasculitis
3. interstitial nephritis
4. necrotizing angiitis

Central Nervous System Reactions:

1. tinnitus and hearing loss
2. paresthesias
3. vertigo
4. dizziness
5. headache
6. blurred vision
7. xanthopsia

Hematologic Reactions:

1. aplastic anemia
2. thrombocytopenia
3. agranulocytosis
4. hemolytic anemia
5. leukopenia
6. anemia
7. eosinophilia

Dermatologic-Hypersensitivity Reactions:

1. toxic epidermal necrolysis
2. Stevens-Johnson Syndrome
3. erythema multiforme
4. drug rash with eosinophilia and systemic symptoms
5. acute generalized exanthematous pustulosis
6. exfoliative dermatitis
7. bullous pemphigoid
8. purpura
9. photosensitivity
10. rash
11. pruritus
12. urticaria

Cardiovascular Reaction:

1. Orthostatic hypotension may occur and be aggravated by alcohol, barbiturates, or narcotics.
2. Increase in cholesterol and triglyceride serum levels

Other Reactions:

1. hyperglycemia
2. glycosuria
3. hyperuricemia
4. muscle spasm
5. weakness
6. restlessness
7. urinary bladder spasm
8. thrombophlebitis
9. fever

Whenever adverse reactions are moderate or severe, furosemide dosage should be reduced or therapy withdrawn.

To report SUSPECTED ADVERSE REACTIONS, contact Hikma Pharmaceuticals USA Inc. at 1-800-962-8364 or FDA at 1-800-FDA-1088 or www.fda.gov/medwatch.

OVERDOSAGE

The principal signs and symptoms of overdose with furosemide are dehydration, blood volume reduction, hypotension, electrolyte imbalance, hypokalemia and hypochloremic alkalosis, and are extensions of its diuretic action.

The acute toxicity of furosemide has been determined in mice, rats and dogs. In all three, the oral LD50exceeded 1000 mg/kg body weight, while the intravenous LD50ranged from 300 to 680 mg/kg.

The acute intragastric toxicity in neonatal rats is 7 to 10 times that of adult rats.

The concentration of furosemide in biological fluids associated with toxicity or death is not known.

Treatment of overdosage is supportive and consists of replacement of excessive fluid and electrolyte losses. Serum electrolytes, carbon dioxide level and blood pressure should be determined frequently. Adequate drainage must be assured in patients with urinary bladder outlet obstruction (such as prostatic hypertrophy).

Hemodialysis does not accelerate furosemide elimination.

DOSAGE AND ADMINISTRATION

Edema

Therapy should be individualized according to patient response to gain maximal therapeutic response and to determine the minimal dose needed to maintain that response.

Adults:

The usual initial dose of furosemide is 20 mg to 80 mg given as a single dose. Ordinarily a prompt diuresis ensues. If needed, the same dose can be administered 6 to 8 hours later or the dose may be increased. The dose may be raised by 20 mg or 40 mg and given not sooner than 6 to 8 hours after the previous dose until the desired diuretic effect has been obtained. The individually determined single dose should then be given once or twice daily (e.g., at 8 am and 2 pm). The dose of furosemide may be carefully titrated up to 600 mg/day in patients with clinically severe edematous states.

Edema may be most efficiently and safely mobilized by giving furosemide on 2 to 4 consecutive days each week.

When doses exceeding 80 mg/day are given for prolonged periods, careful clinical observation and laboratory monitoring are particularly advisable (See PRECAUTIONS: Laboratory Tests).

Geriatric Patients:

In general, dose selection for the elderly patient should be cautious, usually starting at the low end of the dosing range (See PRECAUTIONS: Geriatric Use).

Pediatric Patients:

The usual initial dose of oral furosemide in pediatric patients is 2 mg/kg body weight, given as a single dose. If the diuretic response is not satisfactory after the initial dose, dosage may be increased by 1 or 2 mg/kg no sooner than 6 to 8 hours after the previous dose. Doses greater than 6 mg/kg body weight are not recommended. For maintenance therapy in pediatric patients, the dose should be adjusted to the minimum effective level.

Hypertension

Therapy should be individualized according to the patient’s response to gain maximal therapeutic response and to determine the minimal dose needed to maintain the therapeutic response.

Adults:

The usual initial dose of furosemide for hypertension is 80 mg, usually divided into 40 mg twice a day. Dosage should then be adjusted according to response. If response is not satisfactory, add other antihypertensive agents.

Changes in blood pressure must be carefully monitored when furosemide is used with other antihypertensive drugs, especially during initial therapy. To prevent excessive drop in blood pressure, the dosage of other agents should be reduced by at least 50% when furosemide is added to the regimen. As the blood pressure falls under the potentiating effect of furosemide, a further reduction in dosage or even discontinuation of other antihypertensive drugs may be necessary.

Geriatric Patients:

In general, dose selection and dose adjustment for the elderly patient should be cautious, usually starting at the low end of the dosing range (See PRECAUTIONS: Geriatric Use).

HOW SUPPLIED

Furosemide Tablets, USP

20 mg tablets are supplied as white, flat tablets with beveled edges, product identification “54 840” debossed on one side.

NDC 51655-481-53: Bottle of 10 Tablets

NDC 51655-481-52: Bottle of 30 Tablets

Store and Dispense
Store at 20° to 25°C (68° to 77°F). [See USP Controlled Room Temperature.]

Note:Dispense in a tight, light-resistant, child-resistant container as defined in the USP/NF. Exposure to light may cause slight discoloration. Discolored tablets should not be dispensed.

Protect From Moisture.
PROTECT FROM LIGHT.

Distributed by:
Hikma Pharmaceuticals USA Inc.

Berkeley Heights, NJ 07922

C50000360/03

Revised August 2025

Principal Display Panel

NDC: 51655-481-52